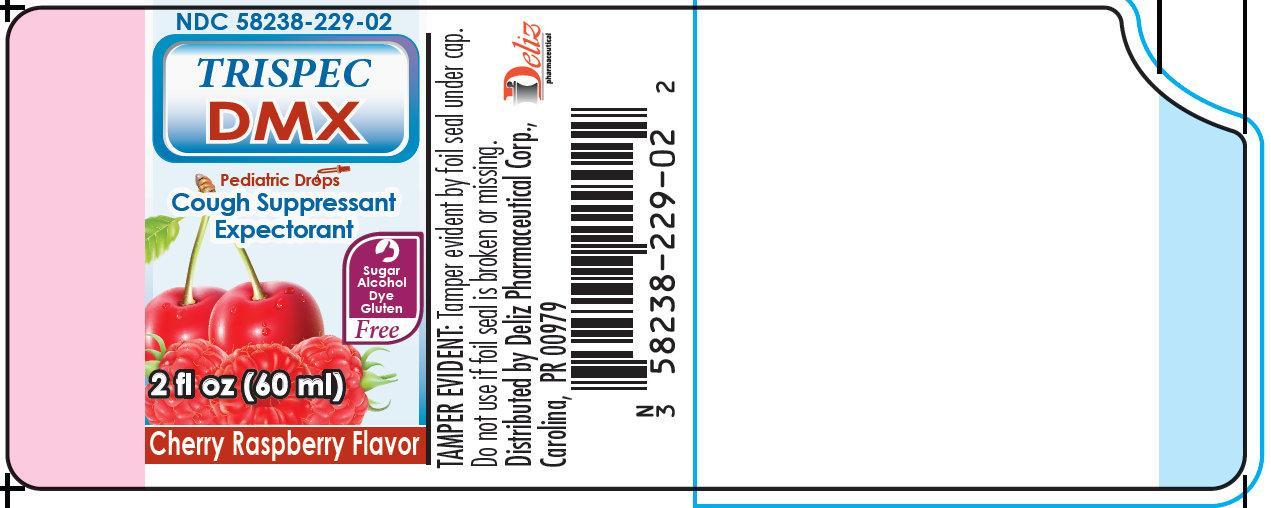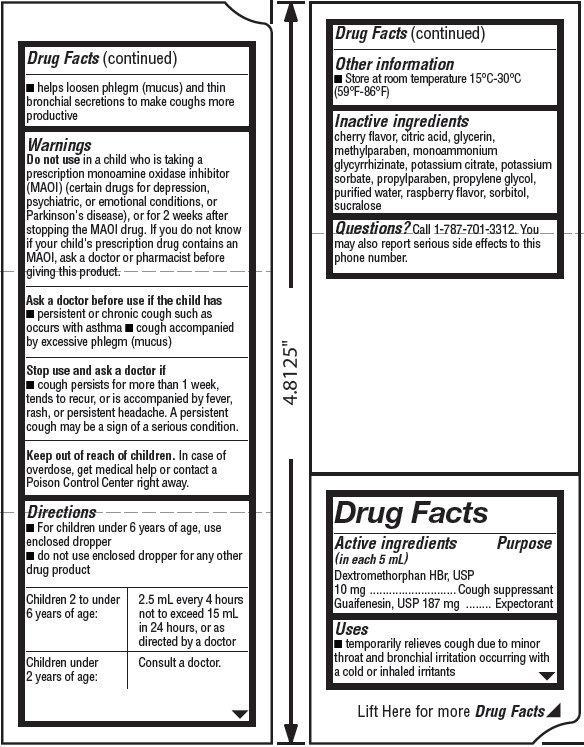 DRUG LABEL: TRISPEC DMX Pediatric Drops Cough Suppressant Expectorant CHERRY RASPBERRY Flavor
NDC: 58238-229 | Form: LIQUID
Manufacturer: Deliz Pharmaceutical Corp
Category: otc | Type: HUMAN OTC DRUG LABEL
Date: 20140227

ACTIVE INGREDIENTS: DEXTROMETHORPHAN HYDROBROMIDE 10 mg/5 mL; GUAIFENESIN 187 mg/5 mL
INACTIVE INGREDIENTS: CITRIC ACID MONOHYDRATE; GLYCERIN; METHYLPARABEN; AMMONIUM GLYCYRRHIZATE; POTASSIUM CITRATE; POTASSIUM SORBATE; PROPYLPARABEN; PROPYLENE GLYCOL; WATER; SORBITOL; SUCRALOSE

TRISPEC DMX Pediatric Drops Cough Suppressant Expectorant CHERRY RASPBERRY Flavor

Active ingredients (in each 5 mL teaspoonful)

Dextromethorphan HBr, USP 10 mg
Guaifenesin, USP 187 mg

Purpose

Cough suppressant
Expectorant

Uses

- temporarily relieves cough due to minor throat and bronchial irritation occurring with a cold or inhaled irritants
- helps loosen phlegm (mucus) and thin bronchial secretions to make coughs more productive

Warnings

Do not use

in a child who is taking a prescription monoamine oxidase inhibitor (MAOI) (certain drugs for depression, psychiatric, or emotional conditions, or Parkinson's disease), or for 2 weeks after stopping the MAOI drug. If you do not know if your child's prescription drug contains an MAOI, ask a doctor or pharmacist before giving this product.

Ask a doctor before use if the child has

- persistent or chronic cough such as occurs with asthma
- cough accompanied by excessive phlegm (mucus)

Stop use and ask a doctor if

- cough persists for more than 1 week, tends to recur, or is accompanied by fever, rash, or persistent headache. A persistent cough may be a sign of a serious condition.

Keep out of reach of children.

In case of overdose, get medical help or contact a Poison Control Center right away.

Directions

- For children under 6 years of age, use enclosed dropper
- do not use enclosed dropper for any other drug product

Children 2 to under 6 years of age: | 2.5 mL every 4 hours not to exceed 15 mL in 24 hours, or as directed by a doctor
Children under 2 years of age: | Consult a doctor.

Other information

- Store at room temperature 15°C-30°C (59°F-86°F)

Inactive ingredients

cherry flavor, citric acid, glycerin, methylparaben, monoammonium glycyrrhizinate, potassium citrate, potassium sorbate, propylparaben, propylene glycol, purified water, raspberry flavor, sorbitol, sucralose

Questions?

Call 1-787-701-3312. You may also report serious side effects to this phone number.